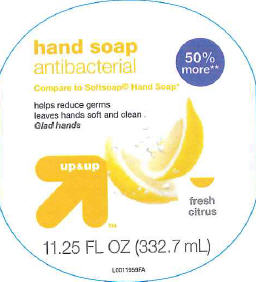 DRUG LABEL: Fresh Citrus
NDC: 11673-954 | Form: SOAP
Manufacturer: Target Corp.
Category: otc | Type: HUMAN OTC DRUG LABEL
Date: 20110331

ACTIVE INGREDIENTS: TRICLOSAN .115 kg/100 L
INACTIVE INGREDIENTS: WATER; SODIUM LAURETH SULFATE; SODIUM LAURYL SULFATE; COCAMIDOPROPYL BETAINE; METHYL GLUCETH-10; SODIUM CHLORIDE; SODIUM HYDROXIDE; BENZYL ALCOHOL; SHEA BUTTER; MANNITOL; MICA; TRIETHYL CITRATE; TITANIUM DIOXIDE

Drug Facts

Active ingredient
Triclosan (0.115%

Purpose
Antibacterial

INDICATIONS AND USAGE

Use for handwashing to decrease bacteria on the skin

Warnings
For external use only-hands only

When using this product
• do not get into eyes. If contact occurs, rinse eyes thoroughly with water.

Keep out of reach of children. If swallowed, get medical help or contact a Poison Control Center right away

DOSAGE AND ADMINISTRATION

Directions •wet hands •apply palmful to hands •scrub thoroughly •rinse thoroughly

INACTIVE INGREDIENT

Inactive ingredients water, sodium laureth sulfate, sodium lauryl sulfate, acrylates copolymer, cocamidopropyl betaine, methyl gluceth-10, PPG-10 methyl glucose ether, fragrance, sodium chloride, cocamide MEA, sodium hydroxide, benzyl alcohol, butyrospermum parkii (shea butter), tetrasodium EDTA, mannitol, cellulose, mica, acrylates/ammonium methacrylate copolymer, triethyl citrate, citric acid, titanium dioxide, iron oxides, alumina, hydroxypropyl methylcellulose, yellow 5, red 33

Made in the USA with US and foreign components
This product is not manufactured or distributed by Colgate-Polmolive Company, distributor of Softsoap Kitchen Fresh Hands Antibacterial Hand Soap
50% more than the 7.5 FL OZ size.

ADVERSE REACTIONS

Dist by Target Corp
Mpls,MN 55403

PACKAGE LABEL

hand soap
antibacterial
Compare to Softsoap Hand Soap
50% more
Helps reduce germs
leaves hand soft and clean
Glad hands
up + up
fresh
citrus
11.25 FL OZ (332.7 mL)